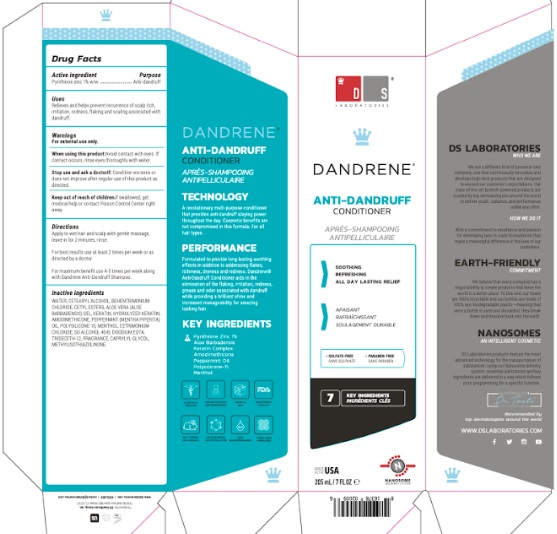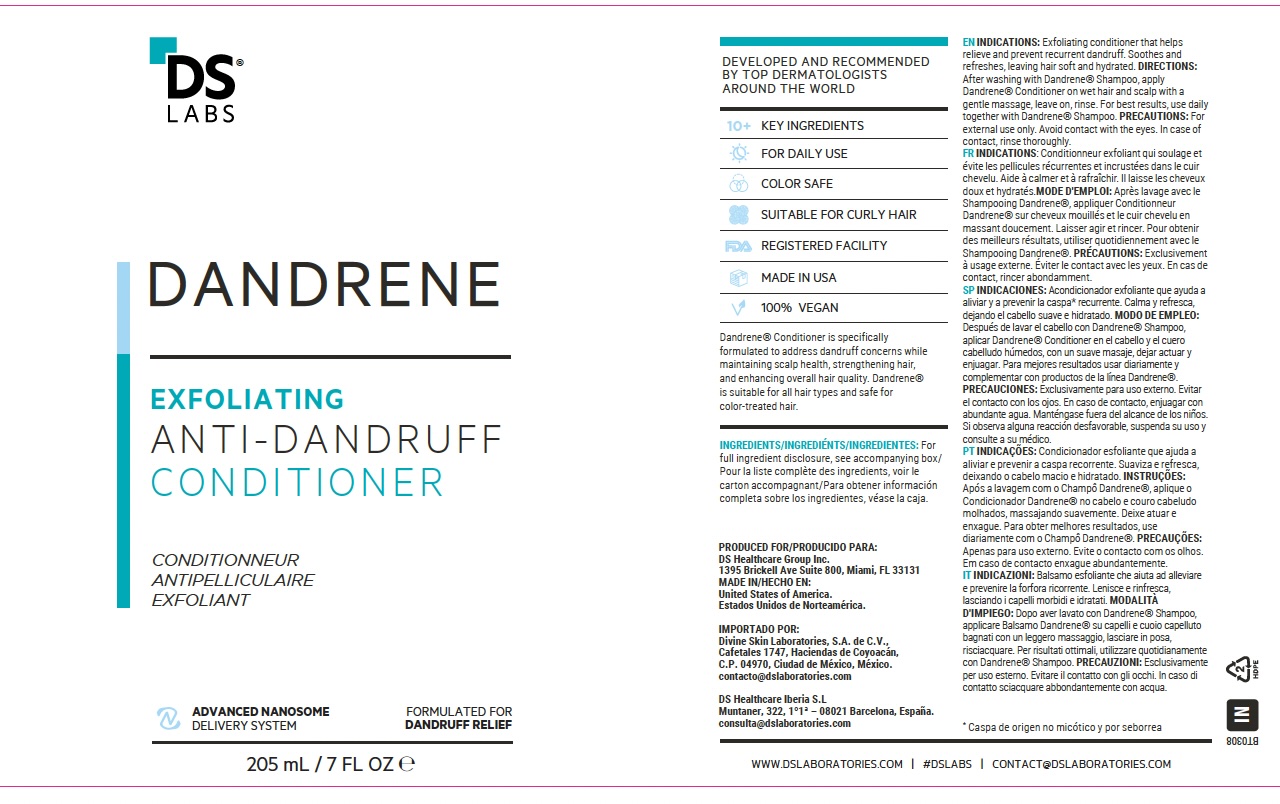 DRUG LABEL: Dandrene Anti-Dandruff Conditioner
NDC: 69188-300 | Form: LOTION
Manufacturer: DS Healthcare Group, Inc.
Category: otc | Type: HUMAN OTC DRUG LABEL
Date: 20251111

ACTIVE INGREDIENTS: PYRITHIONE ZINC 1 g/100 mL
INACTIVE INGREDIENTS: WATER; CETOSTEARYL ALCOHOL; BEHENTRIMONIUM CHLORIDE; CETYL ESTERS WAX; ALOE VERA LEAF; KERATIN, TYPE I CYTOSKELETAL 40; HYDROLYZED SHEEP WOOL KERATIN (200 MW); AMODIMETHICONE (800 CST); PEPPERMINT OIL; POLYSILICONE-15; MENTHOL; CETRIMONIUM CHLORIDE; ALCOHOL; EDETATE DISODIUM ANHYDROUS; TRIDECETH-12; CAPRYLYL GLYCOL; METHYLISOTHIAZOLINONE

Active ingredient

Zinc Pyrithione 1%

Purpose

Anti-dandruff

Uses

Relieves and helps prevent recurrence of scalp itch, irritation, redness, flaking and scaling associated with dandruff

Warnings

For external use only.

When using this Product: Avoid contact with eyes, If contact occurs, rinse eyes thoroughly with water

Stop use and ask a doctor if Condition worsens or does not improve after regular use of this product as directed

Keep out of reach of children. If swallowed, get medical help or contact Poison Control Center right away

Directions

Apply to wet hair and scalp with gentle massage, leave in for 2 minutes, rinse

For best results use atleast 2 times per week or as direacted by a doctor

For maximum benefits use 4-5 times a week along with Dandrene anti-dandruff shampoo

Inactive ingredients

WATER, CETEARYL ALCOHOL, BEHENTRIMONIUM CHLORIDE, CETYL ESTERS, ALOE VERA GEL, KERATIN, HYDROLYZED KERATIN, AMODIMETHICONE, PEPPERMINT OIL, POLYSILICONE-15, MENTHOL, CETRIMONIUM CHLORIDE, SD ALCOHOL 40-B, DISODIUM EDTA, TRIDECETH-12, CAPRYLYL GLYCOL, METHYLISOTHIAZOLINONE